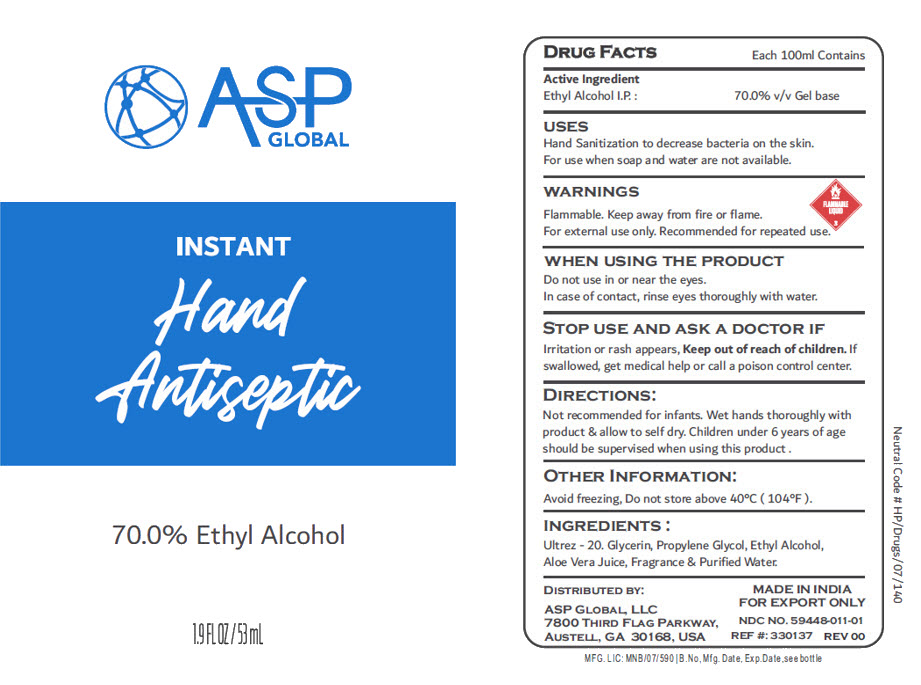 DRUG LABEL: ETHYL ALCOHOL
NDC: 59448-011 | Form: GEL
Manufacturer: ASP Global LLC
Category: otc | Type: HUMAN OTC DRUG LABEL
Date: 20250402

ACTIVE INGREDIENTS: ALCOHOL 70 mL/100 mL
INACTIVE INGREDIENTS: Water; Aloe Vera Leaf; Glycerin; Propylene Glycol; ACRYLATES/C10-30 ALKYL ACRYLATE CROSSPOLYMER (60000 MPA.S AT 0.5%); FRAGRANCE 13576

ETHYL ALCOHOL GEL

DRUG FACTS

Each 100ml Contains

Active ingredient

Ethyl Alcohol I.P. :

PURPOSE

70.0% v/v Gel base

USES

Hand Sanitization to decrease bacteria on the skin.

For use when soap and water are not available.

WARNINGS

Flammable. Keep away from fire or flame.

For external use only. Recommended for repeated use.

WHEN USING THE PRODUCT

Do not use in or near the eyes.

In case of contact, rinse eyes thoroughly with water.

STOP USE AND ASK A DOCTOR IF

KEEP OUT OF REACH OF CHILDREN

Irritation or rash appears, Keep out of reach of children. If swallowed, get medical help or call a poison control center.

DIRECTIONS

Not recommended for infants. Wet hands thoroughly with product & allow to self dry. Children under 6 years of age should be supervised when using this product.

OTHER INFORMATION

Avoid freezing, Do not store above 40°C (104°F).

INGREDIENTS

Ultrez - 20. Glycerin, Propylene Glycol, Ethyl Alcohol, Aloe Vera Juice, Fragrance & Purified Water.

DISTRIBUTED BY:

ASP GLOBAL, LLC
7800 THIRD FLAG PARKWAY,
AUSTELL, GA 30168, USA

PRINCIPAL DISPLAY PANEL - 53 mL Bottle Label

ASP
GLOBAL

INSTANT

Hand
Antiseptic

70.0% Ethyl Alcohol

1.9 FL OZ / 53 mL